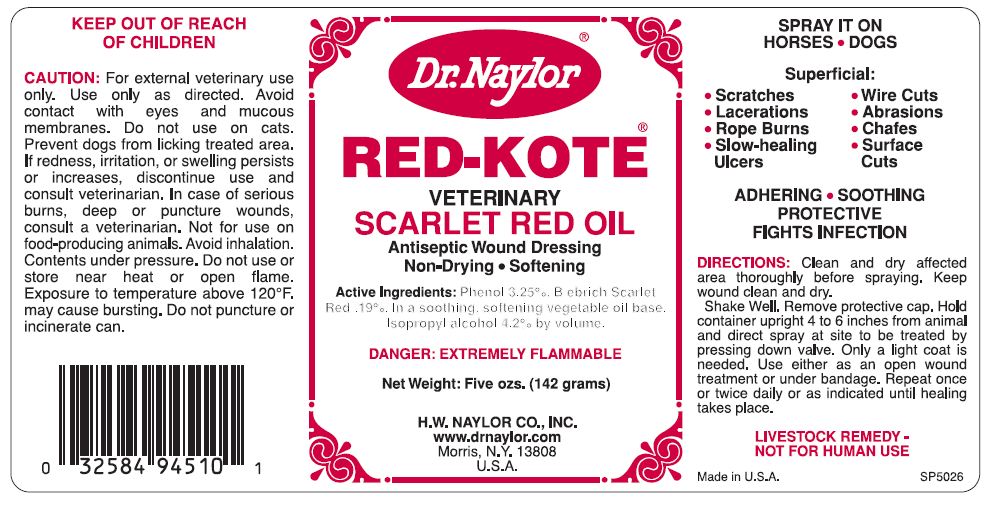 DRUG LABEL: RED-KOTE Veterinary Scarlet-Red Oil 
NDC: 15878-233 | Form: AEROSOL, SPRAY
Manufacturer: H. W. Naylor Company Inc.
Category: animal | Type: OTC ANIMAL DRUG LABEL
Date: 20130104

ACTIVE INGREDIENTS: Phenol 3.25 g/100 g; Scarlet Red .19 g/100 g
INACTIVE INGREDIENTS: Linseed Oil; Castor Oil; Isopropyl Alcohol

RED-KOTE® VETERINARY SCARLET RED OIL

Active Ingredients

Phenol 3.25%, Biebrich Scarlet Red .19%.

Purpose

Antiseptic Wound Dressing for Horses and Dogs for Superficial:

- Scratches
- Lacerations
- Rope Burns
- Slow-healing Ulcers
- Wire Cuts
- Abrasions
- Chafes
- Surface Cuts

Directions

Clean and dry affected area thoroughly before spraying. Keep wound clean and dry.

Shake Well. Remove protective cap. Hold container upright 4 to 6 inches from animal and direct spray at site to be treated by pressing down valve. Only a light coat is needed. Use either as an open wound treatment or under bandage. Repeat once or twice daily or as indicated until healing takes place.

Safety

LIVESTOCK REMEDY - NOT FOR HUMAN USE

CAUTION: For external veterinary use only. Use only as directed. Avoid contact with eyes and mucous membranes. Do not use on cats. Prevent dogs from licking treated area.

If redness, irritation, or swelling persists or increases, discontinue use and consult veterinarian.

In case of serious burns, deep or puncture wounds, consult a veterinarian.

Not for use on food-producing animals.

Avoid inhalation.

Contents under pressure.

Do not use or store near heat or open flame.

Exposure to temperature above 120° F. may cause bursting.

Do not puncture or incinerate can.

Other Ingredients

Vegetable Oil Base, Isopropyl Alcohol

Questions?

www.drnaylor.com

Principal Display Panel

Dr. Naylor®
RED-KOTE® VETERINARY SCARLET RED OIL
Antiseptic Wound Dressing
Non-Drying ● Softening
DANGER: EXTREMELY FLAMMABLE
Net Weight: Five ozs. (142 grams)
H.W. NAYLOR CO., INC.
www.drnaylor.com
Morris N.Y. 13808
U.S.A.
Made in U.S.A.
SP5026